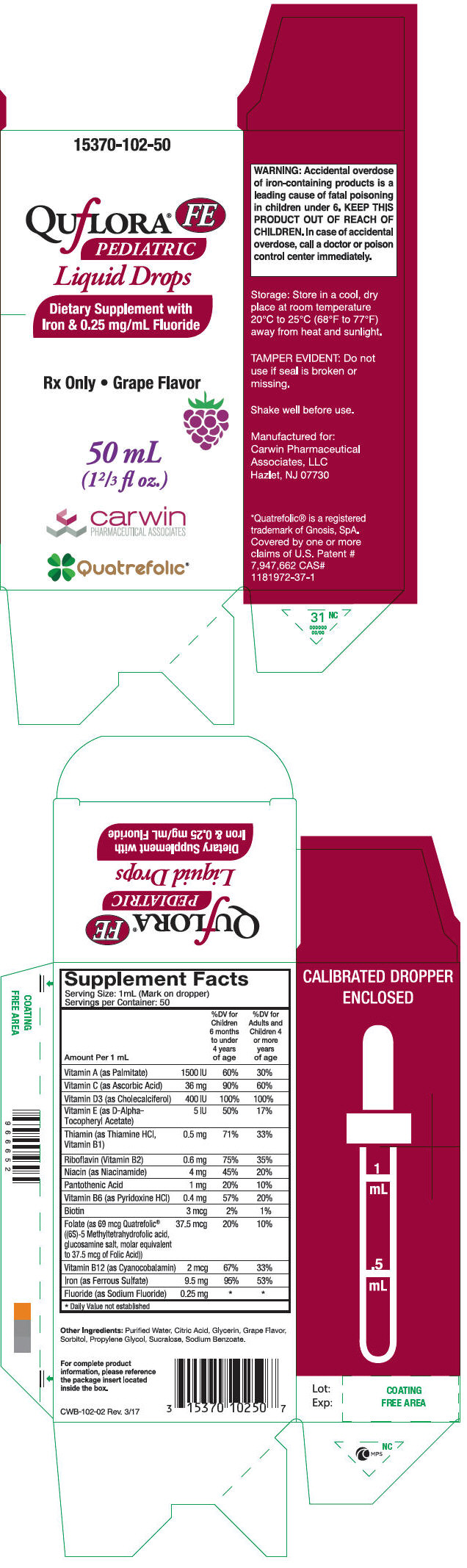 DRUG LABEL: Quflora FE Pediatric Drops
NDC: 15370-102 | Form: LIQUID
Manufacturer: Carwin Pharmaceutical Associates, LLC
Category: prescription | Type: HUMAN PRESCRIPTION DRUG LABEL
Date: 20170419

ACTIVE INGREDIENTS: VITAMIN A PALMITATE 1500 [iU]/1 mL; ASCORBIC ACID 36 mg/1 mL; CHOLECALCIFEROL 400 [iU]/1 mL; .ALPHA.-TOCOPHEROL ACETATE, D- 5 [iU]/1 mL; THIAMINE HYDROCHLORIDE 0.5 mg/1 mL; RIBOFLAVIN 0.6 mg/1 mL; NIACINAMIDE 4 mg/1 mL; PANTOTHENIC ACID 1 mg/1 mL; PYRIDOXINE HYDROCHLORIDE 0.4 mg/1 mL; BIOTIN 3 ug/1 mL; LEVOMEFOLATE GLUCOSAMINE 37.5 ug/1 mL; CYANOCOBALAMIN 2 ug/1 mL; FERROUS SULFATE 9.5 mg/1 mL; SODIUM FLUORIDE 0.25 mg/1 mL
INACTIVE INGREDIENTS: WATER; CITRIC ACID MONOHYDRATE; GLYCERIN; SORBITOL; PROPYLENE; SUCRALOSE; SODIUM BENZOATE

Quflora® FE Pediatric Liquid Drops

DESCRIPTION

Supplement Facts
Serving Size: 1 mL (Mark on dropper)
Servings per Container: 50
Amount Per 1 mL |  | % DV Children 6 months to under 4 years of age | % DV for Adults and Children 4 or more years of age
Vitamin A (as Palmitate) | 1500 IU | 60% | 30%
Vitamin C (as Ascorbic Acid) | 36 mg | 90% | 60%
Vitamin D3 (as Cholecalciferol) | 400 IU | 100% | 100%
Vitamin E (as D-Alpha-Tocopheryl Acetate) | 5 IU | 50% | 17%
Thiamin (as Thiamine HCl, Vitamin B1) | 0.5 mg | 71% | 33%
Riboflavin (Vitamin B2) | 0.6 mg | 75% | 35%
Niacin (as Niacinamide) | 4 mg | 45% | 20%
Pantothenic Acid | 1 mg | 20% | 10%
Vitamin B6 (as Pyridoxine HCl) | 0.4 mg | 57% | 20%
Biotin | 3 mcg | 2% | 1%
Folate (as 69 mcg Quatrefolic® ((6S)-5 Methyltetrahydrofolic acid, glucosamine salt, molar equivalent to 37.5 mcg of Folic Acid)) | 37.5 mcg | 20% | 10%
Vitamin B12 (as Cyanocobalamin) | 2 mcg | 67% | 33%
Iron (as Ferrous Sulfate) | 9.5 mg | 95% | 53%
Fluoride (as Sodium Fluoride) | 0.25 mg | [Daily Value not established]

Other Ingredients: Purified Water, Citric Acid, Glycerin, Grape Flavor, Sorbitol, Propylene Glycol, Sucralose, Sodium Benzoate.

INDICATIONS AND USAGE

Quflora® FE Pediatric Liquid Drops is a prescription dietary supplement providing essential vitamins, iron and fluoride.

CONTRAINDICATIONS

Do not use in areas where drinking water exceeds 0.6 ppm F. Do not administer to pediatric patients less than 6 months old.

PRECAUTIONS

General

Do not use this product if you are allergic to any of the ingredients. The suggested dose should not be exceeded, since dental fluorosis may result from continued ingestion of large amounts of fluoride. Do not eat or drink dairy products within one hour of fluoride administration since these may decrease effectiveness.

Folic Acid

Folic Acid alone is improper therapy in the treatment of pernicious anemia and other megaloblastic anemias where vitamin B12 is deficient. Folic acid in doses above 0.1 mg daily may obscure pernicious anemia in that hematologic remission can occur while neurological manifestations progress.

WARNING

Accidental overdose of iron-containing products is a leading cause of fatal poisoning in children under 6. KEEP THIS PRODUCT OUT OF REACH OF CHILDREN. In case of accidental overdose, call a doctor or poison control center immediately.

Other information

Call your doctor for medical advice about side effects. You may report serious side effects or obtain product information by calling Carwin Pharmaceutical Associates, LLC at 1-844-700-5011.

DOSAGE AND ADMINISTRATION

See schedule below to determine dosage. Administer orally as prescribed by a healthcare practitioner. Use with calibrated dropper for measuring doses. Each dropper full 1mL contains: 0.55 mg sodium fluoride, USP.

Fluoride Ion Level In Drinking Water (ppm) [1.0 part per million (ppm) = 1 milligram/liter (mg/L)]
Age | Less than 0.3ppm | 0.3-0.6 ppm | Greater than 0.6 ppm
Birth-6 months | None | None | None
6 months-3 years | 0.25 mg/day [2.2 mg sodium fluoride contains 1 mg fluoride ion] | None | None
3-6 years | 0.50 mg/day | 0.25 mg/day | None
6-16 years | 1.0 mg/day | 0.50 mg/day | None

Dietary Fluoride Supplement dosing schedule approved by the American Dental Association (ADA), American Academy of Pediatrics (AAP) & American Academy of Pediatric Dentistry (AAPD).

DESCRIPTION

Quflora® FE Pediatric Liquid Drops is a yellow, dye free, grape flavored liquid.

HOW SUPPLIED

Quflora® FE Pediatric Liquid Drops in a 50 mL (1 ⅔ fl. oz.) child-resistant bottle with accompanying calibrated dropper. (Product Code: 15370-102-50).

Rx Only

STORAGE

Store in a cool, dry place at room temperature 20°C to 25°C (68°F to 77°F) away from heat and sunlight.

SHAKE WELL BEFORE USING

TAMPER EVIDENT

Do not use if seal is broken or missing.

Quatrefolic® is a registered trademark of Gnosis, SpA. Covered by one or more claims of U.S. Patent # 7,947,662 CAS# 1181972-37-1

Manufactured for:
Carwin Pharmaceutical Associates, LLC
Hazlet, NJ 07730
www.carwinpharma.com

Rev. 3/17

PRINCIPAL DISPLAY PANEL - 50 mL Bottle Carton

15370-102-50

QUfLORA®
FE
PEDIATRIC
Liquid Drops

Dietary Supplement with
Iron & 0.25 mg/mL Fluoride

Rx Only • Grape Flavor

50 mL
(1⅔ fl oz.)

carwin
PHARMACEUTICAL ASSOCIATES

Quatrefolic®